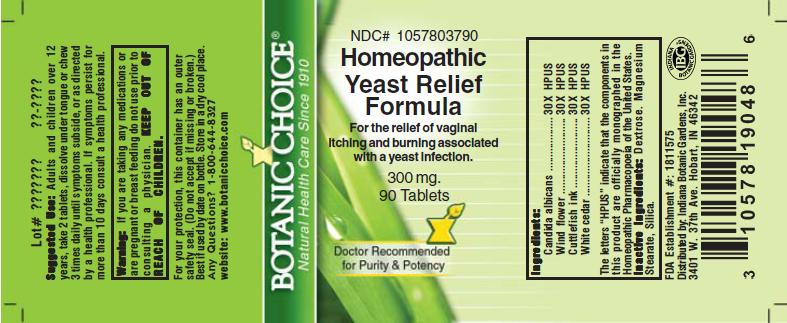 DRUG LABEL: Homeopathic Yeast Relief Formula
NDC: 10578-037 | Form: TABLET
Manufacturer: Indiana Botanic Gardens
Category: homeopathic | Type: HUMAN OTC DRUG LABEL
Date: 20110325

ACTIVE INGREDIENTS: CANDIDA ALBICANS 30 [hp_X]/1 1; PULSATILLA VULGARIS 30 [hp_X]/1 1; THUJA OCCIDENTALIS LEAFY TWIG 30 [hp_X]/1 1; SEPIA OFFICINALIS JUICE 30 [hp_X]/1 1
INACTIVE INGREDIENTS: DEXTROSE; MAGNESIUM STEARATE ; SILICON DIOXIDE 

Homeopathic Yeast Relief Formula

ACTIVE INGREDIENT

I n g r e d i e n t s :

Candida albicans........................ 30X HPUS
Wind flower.................................... 30X HPUS
Cuttlefish ink........................................ 30X HPUS
White cedar...................... 30X HPUS

The letters “HPUS” indicate that the components in
this product are officially monographed in the
Homeopathic Pharmacopoeia of the United States.

PURPOSE

For the relief of vaginal itching and burning associated with a yeast infection

KEEP OUT OF
REACH OF CHILDREN.

INDICATIONS AND USAGE

For the relief of vaginal itching and burning associated with a yeast infection

WARNINGS

Warning: If you are taking any medications or
are pregnant or breast feeding do not use prior to
consulting a physician.

DOSAGE AND ADMINISTRATION

Suggested Use: Adults and children over 12
years, take 2 tablets, dissolve under tongue or
chew 3 times daily until symptoms subside, or as directed by a health care
professional. If symptoms persist for more than 10 days consult a
health professional.

Inactive Ingredients: Dextrose, Magnesium
Stearate, Silica.

PACKAGE LABEL

NDC# 1057803790

Homeopathic Yeast Relief Formula

For the relief of vaginal itching and burning associated with a yeast infection

300 mg.
90 Tablets

USER SAFETY WARNINGS

For your protection, this container has an outer
safety seal. (Do not accept if missing or broken.)
Best if used by date on bottle. Store in a dry cool place.
Any Questions? 1-800-644-8327
website: www.botanicchoice.com

FDA Establishment #: 1811575

Distributed by: Indiana Botanic Gardens, Inc.
3401 W. 37th Ave. Hobart, IN 46342